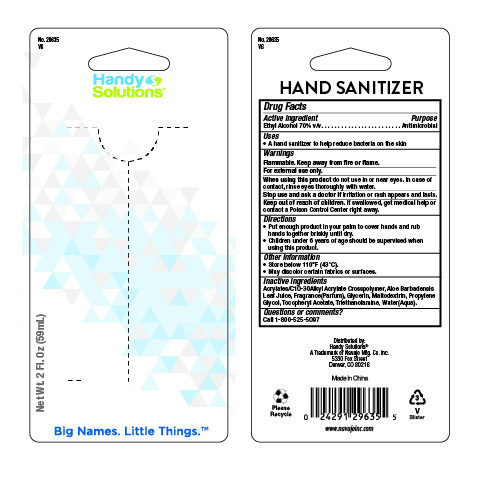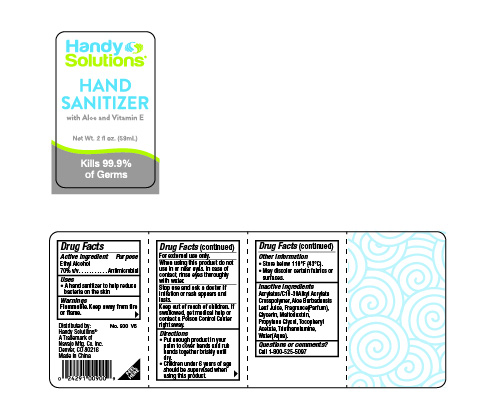 DRUG LABEL: Handy Solutions Hand Sanitizer
NDC: 67751-086 | Form: LIQUID
Manufacturer: Navajo Manufacturing Company Inc.
Category: otc | Type: HUMAN OTC DRUG LABEL
Date: 20240415

ACTIVE INGREDIENTS: ALCOHOL 70 mL/100 mL
INACTIVE INGREDIENTS: MALTODEXTRIN; WATER; ACRYLATES/C10-30 ALKYL ACRYLATE CROSSPOLYMER (60000 MPA.S); GLYCERIN; PROPYLENE GLYCOL; ALPHA-TOCOPHEROL ACETATE; ALOE VERA LEAF; TROLAMINE

Handy Solutions Hand Sanitizer

Active ingredient

Ethyl Alcohol 70% v/v

Purpose

Antimicrobial

Uses

- A hand sanitizer to help reduce bacteria on the skin

Warnings

Flammable. Keep away from fire or flame.

For external use only.

When using this product do not use in or near eyes. In case of contact, rinse eyes thoroughly with water.

Stop use and ask a doctor if irritation or rash appears and lasts.

Keep out of reach of children. If swallowed, get medical help or contact a Poison Control Center right away.

Directions

- Put enough product in your palm to cover hands and rub hands together briskly until dry.
- Children under 6 years of age should be supervised when using this product.

Other information

- Store below 110°F (43°C).
- May discolor certain fabrics or surfaces.

Inactive ingredients

Acrylates/C10-30 Alkyl Acrylate Crosspolymer, Aloe Barbadensis Leaf Juice, Fragrance(Parfum), Glycerin, Maltodextrin, Propylene Glycol, Tocopheryl Acetate, Triethanolamine, Water(Aqua).

Questions or comments?

Call 1-800-525-5097